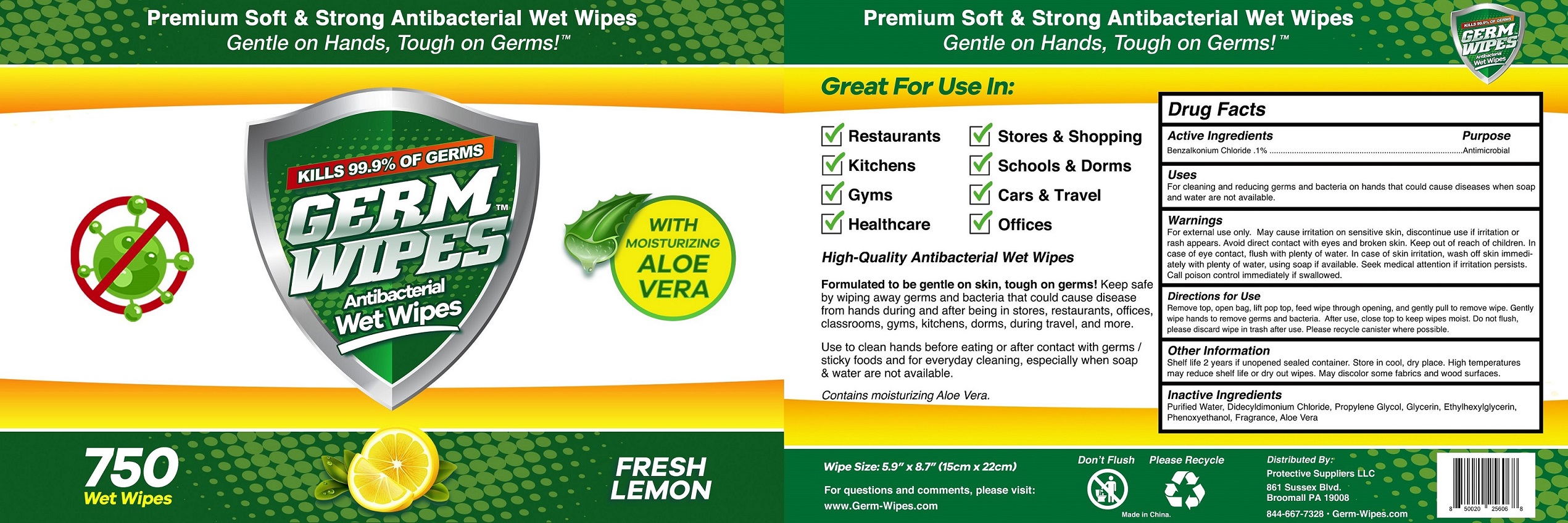 DRUG LABEL: Antibacterial Wet Wipes
NDC: 79953-751 | Form: CLOTH
Manufacturer: Protective Suppliers LLC
Category: otc | Type: HUMAN OTC DRUG LABEL
Date: 20200810

ACTIVE INGREDIENTS: BENZALKONIUM CHLORIDE 0.1 g/100 g
INACTIVE INGREDIENTS: GLYCERIN; FRAGRANCE LEMON ORC2001060; ALOE VERA LEAF; DIDECYLDIMONIUM CHLORIDE; WATER; PROPYLENE GLYCOL; PHENOXYETHANOL; ETHYLHEXYLGLYCERIN

79953-751 Antibacterial Wet Wipes Ningbo Chenxing Daily Necessities Co., Ltd.

Active Ingredient(s)

Benzalkonium Chloride 0.1%. Purpose: Antibacterial

Purpose

Antibacterial, Wet Wipes

Use

For cleaning and reducing germs and bacteria on hand that could cause disease when soap and water are not available.

Warnings

For external use only. Flammable. May cause irritation on sensitive skin,discontinue use if irritation or rash appears.Avoid direct contact with eyes and broken skin. Keep out of reach of children. In case of eye contact , flush with plenty of water. In case of skin irritation, wash off skin immediatelly with plenty of water, using soap if available. Seek medical attention immediately if irritation persists.Call poison control immediately if swallowed.

Do not use

- in children less than 2 months of age
- on open skin wounds

When using this product keep out of eyes, ears, and mouth. In case of contact with eyes, rinse eyes thoroughly with water.
Stop use and ask a doctor if irritation or rash occurs. These may be signs of a serious condition.
Keep out of reach of children. If swallowed, get medical help or contact a Poison Control Center right away.

Stop use and ask a doctor if irritation or rash occurs. These may be signs of a serious condition.

Keep out of reach of children. If swallowed, get medical help or contact a Poison Control Center right away.

Directions

Remove top, open bag,lift pop top,feed wipe through opening, and gently pull to remove wipe. Gently wipe hands to remove germs and becteria. After use, close top to keep wipes moist. Do not flush, please discard wipe in trash after use. Please recycle canister where possible.

Other information

Shelf life 2 years if unopened sealed container. Store in cool, dry place. High temperatures may reduce shelf life or dry out wipes. May discolor some fabrics and wood surface.

Inactive ingredients

Purified water, Didecyldimonium Chloride, Propylene Glycol, Glycerin, Ethylhexyl Glycerin,Phenoxyethanol,Fragrance,Aloe Vera

Package Label - Principal Display Panel

750 WIPES NDC:79953-750-01